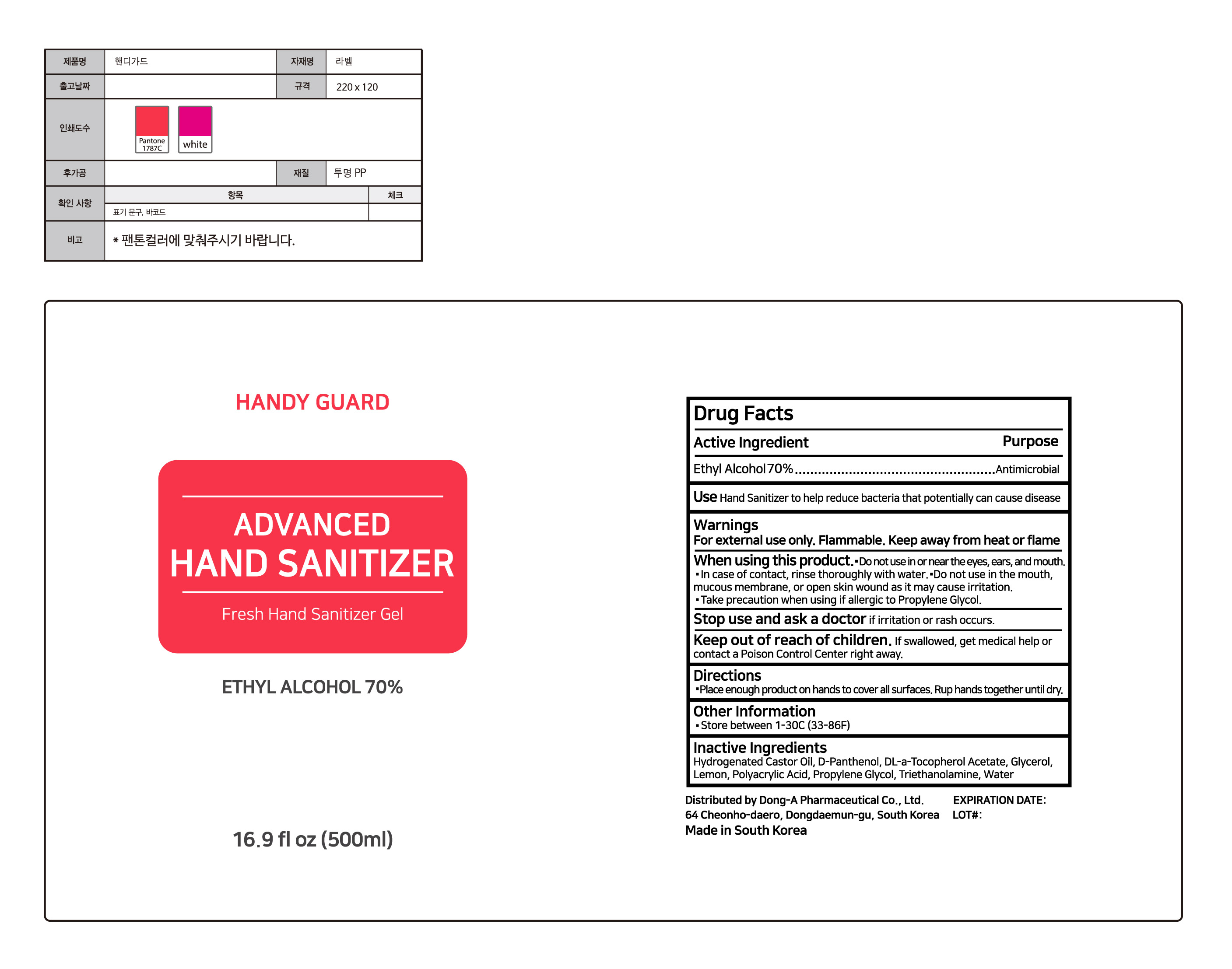 DRUG LABEL: Advanced Hand Sanitizer
NDC: 77973-800 | Form: GEL
Manufacturer: Dong-A Pharmaceutical Co., Ltd.
Category: otc | Type: HUMAN OTC DRUG LABEL
Date: 20200609

ACTIVE INGREDIENTS: ALCOHOL 70 mL/100 mL
INACTIVE INGREDIENTS: DEXPANTHENOL; WATER; TROLAMINE; HYDROGENATED CASTOR OIL; .ALPHA.-TOCOPHEROL ACETATE, DL-; GLYCERIN; PROPYLENE GLYCOL; POLYACRYLIC ACID (250000 MW); LEMON

This is a hand sanitizer manufactured according to the Temporary Policy for Preparation of Certain Alcohol-Based Hand Sanitizer Products During the Public Health Emergency (CoViD-19); Guidance for Industry.

The hand sanitizer is manufactured using only the following United States Pharmacopoeia (USP) grade ingredients in the preparation of the product (percentage in final product formulation) consistent with World Health Organization (WHO) recommendations:

1. Alcohol (ethanol) (USP or Food Chemical Codex (FCC) grade) (80%, volume/volume (v/v)) in an aqueous solution denatured according to Alcohol and Tobacco Tax and Trade Bureau regulations in 27 CFR part 20.
2. Glycerol (1.45% v/v).
3. Hydrogen peroxide (0.125% v/v).
4. Sterile distilled water or boiled cold water.

The firm does not add other active or inactive ingredients. Different or additional ingredients may impact the quality and potency of the product.

Active Ingredient(s)

Ethyl Alcohol 70%

Purpose

Antimicrobial

Use

Hand Sanitizer to help reduce bacteria that potentially can cause disease.

Warnings

For external use only. Flammable. Keep away from heat or flame

Do not use in or near the eyes, ears, and mouth.

In case of contact, rinse thoroughly with water.

Do not use in the mouth, mucous membrane, or open skin wound as it may cause irritation.

Take precaution when using if allergic to Propylene Glycol.

Stop use and ask a doctor if irritation or rash occurs.

Keep out of reach of children. If swallowed, get medical help or contact a Poison Control Center right away.

Directions

- Place enough product on hands to cover all surfaces. Rub hands together until dry.

Other information

- Store between 1-30C (33-86F)

Inactive ingredients

WAter, Triethanolamine, Hydrogenated Castor Oil, Glycerol, Propylene Glycol, D-Panthenol, Polyacrylic Acid, Lemon, DL-alpha-Tocopherol Acetate

Package Label - Principal Display Panel

500 mL NDC: 77973-800-01